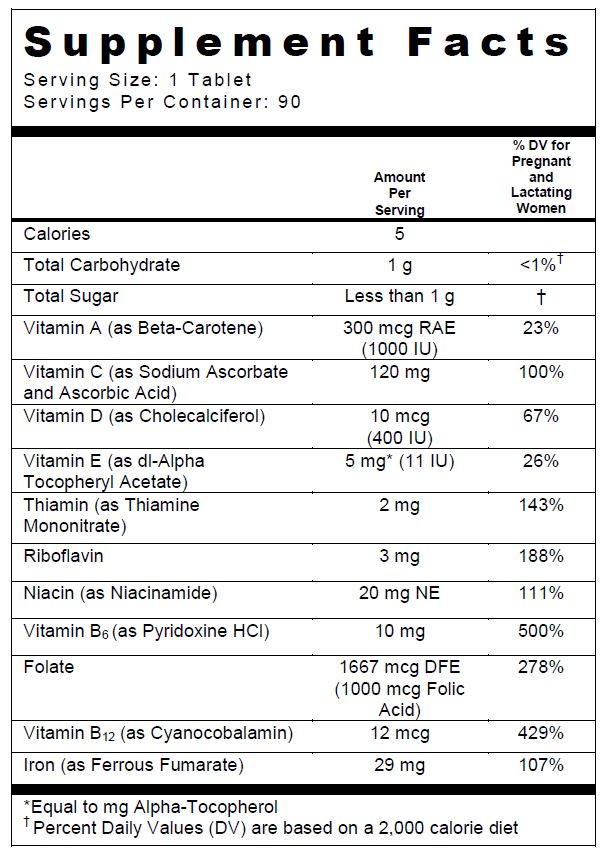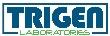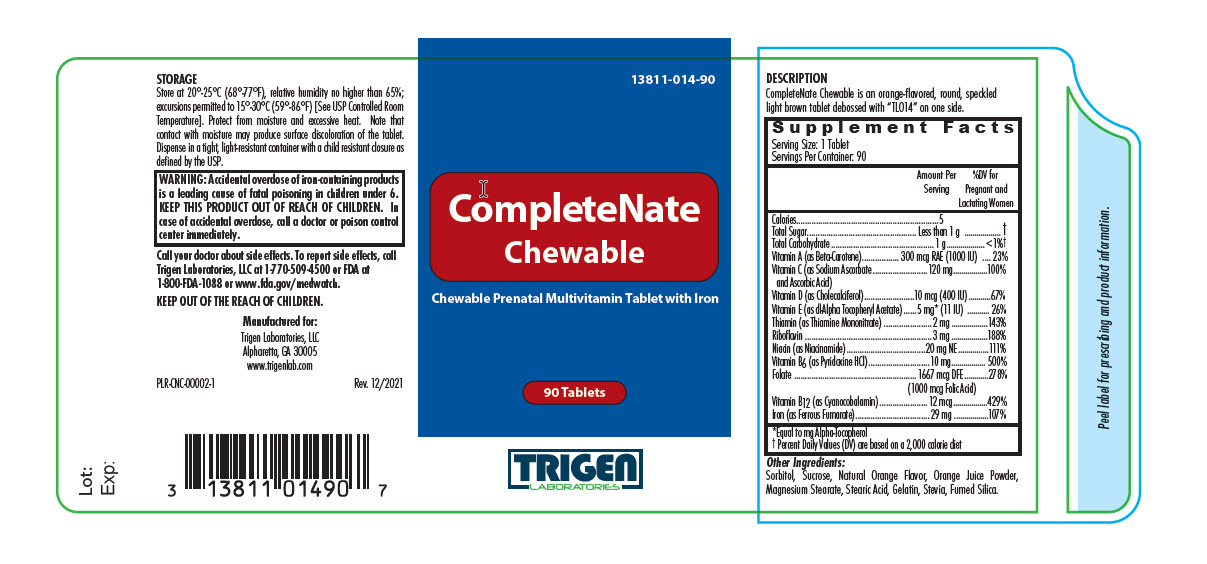 DRUG LABEL: CompleteNate Chewable
NDC: 13811-014 | Form: TABLET
Manufacturer: Trigen Laboratories, LLC
Category: other | Type: DIETARY SUPPLEMENT
Date: 20211229

ACTIVE INGREDIENTS: BETA CAROTENE 1000 [iU]/1 1; ascorbic acid 48 mg/1 1; sodium ascorbate 72 mg/1 1; cholecalciferol 400 [iU]/1 1; .alpha.-tocopherol acetate, dl- 11 [iU]/1 1; thiamine mononitrate 2 mg/1 1; riboflavin 3 mg/1 1; niacinamide 20 mg/1 1; pyridoxine Hydrochloride 10 mg/1 1; folic acid 1 mg/1 1; cyanocobalamin 12 ug/1 1; ferrous fumarate 29 mg/1 1
INACTIVE INGREDIENTS: sorbitol; sucrose; magnesium stearate; stearic acid; gelatin; stevia rebaudiuna leaf; SILICON DIOXIDE; ORANGE OIL; ORANGE

CompleteNate Chewable
Chewable Prenatal Multivitamin Tablet with Iron

SUPPLEMENT FACTS

Other Ingredients: Sorbitol, Sucrose, Natural Orange Flavor, Orange Juice Powder, Magnesium Stearate, Stearic Acid, Gelatin, Stevia, Fumed Silica.

CompleteNate Chewable tablets are formulated to provide vitamin and mineral supplementation throughout pregnancy and during postnatal period, for both the lactating and non-lactating mother. It is also useful for improving nutritional status prior to conception.

CONTRAINDICATIONS

CompleteNate Chewable should not be used by patients with a known hypersensitivity to any of the listed ingredients. All iron compounds are contraindicated in patients with hemochromatosis, hemosiderosis, or hemolytic anemias.

WARNINGS

WARNING: Accidental overdose of iron-containing products is a leading cause of fatal poisoning in children under 6. KEEP THIS PRODUCT OUT OF REACH OF CHILDREN. In case of accidental overdose, call a doctor or poison control center immediately.

PRECAUTIONS

Folic acid alone is improper therapy in the treatment of pernicious anemia and other megaloblastic anemias where vitamin B12 is deficient. Folic acid in doses above 0.1 mg daily may obscure pernicious anemia, in that hematologic remission can occur while neurological manifestations remain progressive.

Pediatric Use: Safety and effectiveness in pediatric patients have not been established.

Geriatric Use: Safety and effectiveness in elderly patients have not been established.

DRUG INTERACTIONS

CompleteNate Chewable Tablets is not recommended for and should not be given to patients receiving levodopa because the action of levodopa is antagonized by pyridoxine. There is a possibility of increased bleeding due to pyridoxine interaction with anticoagulants (e.g., Aspirin, Heparin, Clopidogrel).

ADVERSE REACTIONS

Folic Acid: Allergic sensitizations have been reported following both oral and parenteral administration of folic acid.

Ferrous Fumarate: Gastrointestinal disturbances (anorexia, nausea, diarrhea, constipation) occur occasionally, but are usually mild and may subside with continuation of therapy and physician encouragement. Although the absorption of iron is best when taken between meals, occasional G.I. disturbances may be controlled by giving CompleteNate Chewable shortly after meals.

The patient’s medical conditions and consumption of other drugs, herbs, and/or supplements should be considered.

OVERDOSAGE

Iron is toxic. When overdoses are ingested by children, severe reactions, including fatalities, have resulted. CompleteNate Chewable should be stored beyond the reach of children to protect against accidental iron poisoning.

DESCRIPTION

CompleteNate Chewable is an orange-flavored, round, speckled light brown tablet debossed with “TL014” on one side.

DIRECTIONS FOR USE

Take one tablet by mouth daily or as directed by a physician.

HOW SUPPLIED

CompleteNate Chewable is supplied in bottles of 90 tablets.

PRODUCT CODE 13811-014-90

STORAGE

Store at 20°-25°C (68°-77°F), relative humidity no higher than 65%; excursions permitted to 15°-30°C (59°-86°F) [See USP Controlled Room Temperature]. Protect from moisture and excessive heat. Note that contact with moisture may produce surface discoloration of the tablet. Dispense in a tight, light-resistant container with a child resistant closure as defined by the USP.

KEEP OUT OF REACH OF CHILDREN.

For use on the order of a healthcare practitioner.

Call your doctor about side effects. To report side effects, call Trigen Laboratories, LLC at 1-770-509-4500 or FDA at 1-800-FDA-1088 or www.fda.gov/medwatch.

PLR-CNC-00002-1 Rev. 12/2021

Manufactured for:

Trigen Laboratories, LLC

Alpharetta, GA 30005

www.trigenlab.com

PRINCIPAL DISPLAY PANEL - 90 Tablet Bottle Label

13811-014-90

90 Tablets

CompleteNate
Chewable

Chewable Prenatal Multivitamin Tablet with Iron

TRIGEN
LABORATORIES